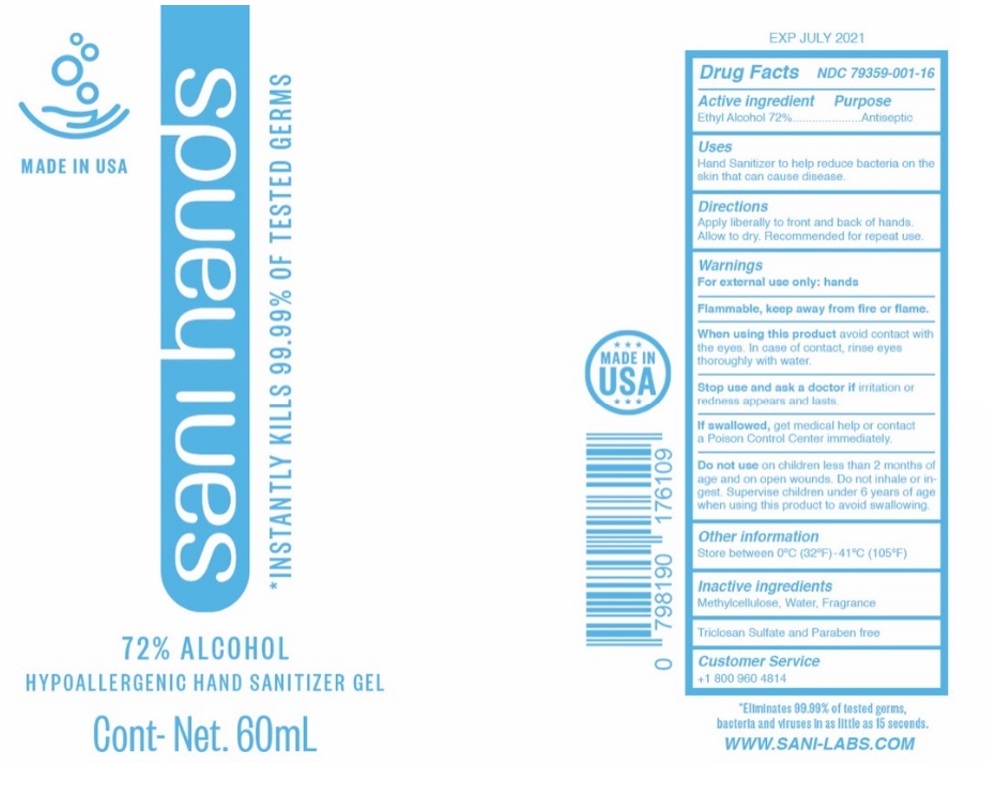 DRUG LABEL: sani hands
NDC: 79359-001 | Form: GEL
Manufacturer: Maine Craft Distilling, LLC
Category: otc | Type: HUMAN OTC DRUG LABEL
Date: 20200723

ACTIVE INGREDIENTS: ALCOHOL 72 mL/100 mL
INACTIVE INGREDIENTS: METHYLCELLULOSE, UNSPECIFIED; WATER

sani hands HYPOALLERGENIC HAND SANITIZER GEL

Active ingredient

Ethyl Alcohol 72%

Purpose

Antiseptic

Uses

Hand Sanitizer to help reduce bacteria on the skin that can cause disease.

Directions

Apply liberally to front and back of hands.

Allow to dry. Recommended for repeat use.

Warnings

For external use only: hands

Flammable, keep away from fire or flame.

When using this product avoid contact with the eyes. In case of contact, rinse eyes thoroughly with water.

Stop use and ask a doctor if irritation or redness appears and lasts.

Do not use on children less than 2 months of age and on open wounds. Do not inhale or ingest.

Supervise children under 6 years of age when using this product to avoid swallowing

KEEP OUT OF REACH OF CHILDREN

If swallowed, get medical help or contact a Poison Control Center immediately.

Other information

Store between 0ºC (32ºF) - 41ºC (105ºF)

Inactive ingredients

Methylcellulose, water, Fragrance

Customer Service

+1 800 960 4814

MADE IN USA

*INSTANTLY KILLS 99.99% OF TESTED GERMS

72% ALCOHOL

Triclosan Sulfate and Paraben free

*Eliminates 99.99% of tested germs, bacteria and viruses in as little as 15 seconds.

WWW.SANI-LABS.COM